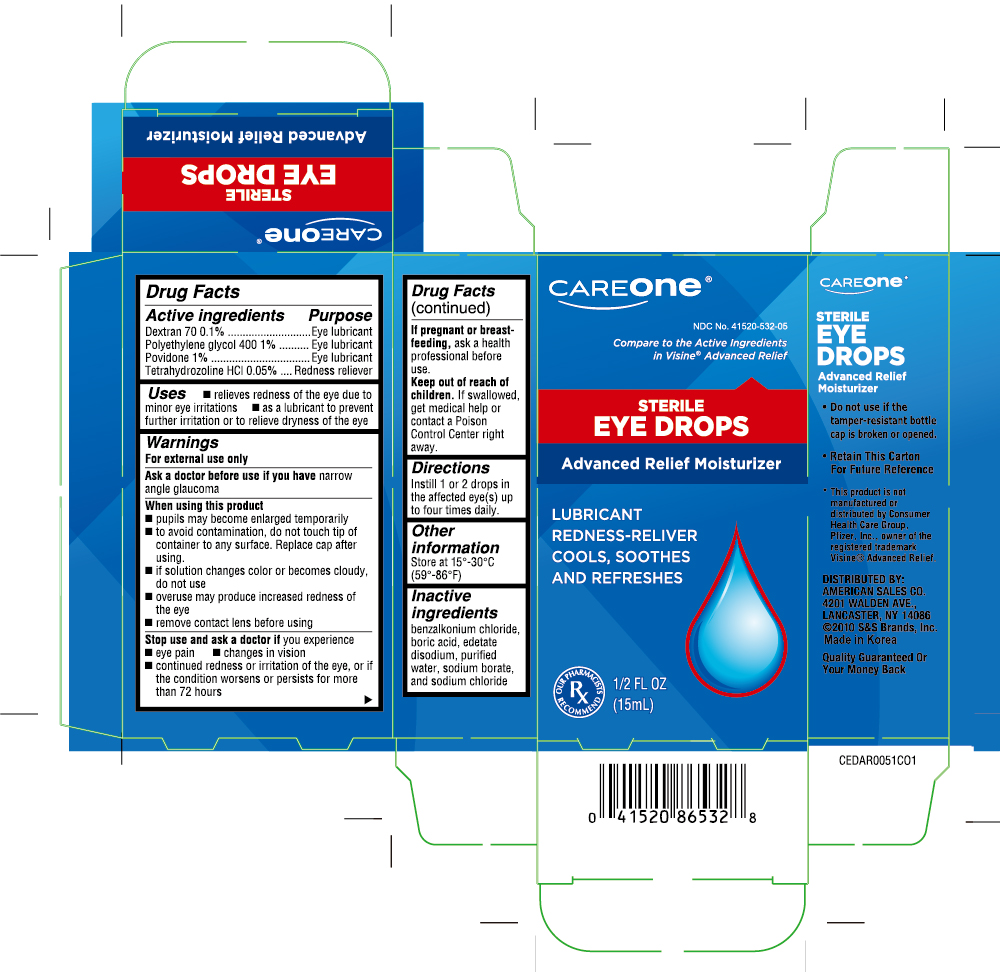 DRUG LABEL: Advanced relief
NDC: 41520-532 | Form: LIQUID
Manufacturer: American Sales Company
Category: otc | Type: HUMAN OTC DRUG LABEL
Date: 20241231

ACTIVE INGREDIENTS: TETRAHYDROZOLINE HYDROCHLORIDE 0.5 mg/1 mL; DEXTRAN 70 1 mg/1 mL; POLYETHYLENE GLYCOL 400 10 mg/1 mL; POVIDONE 10 mg/1 mL
INACTIVE INGREDIENTS: BENZALKONIUM CHLORIDE; BORIC ACID; EDETATE DISODIUM; WATER; SODIUM BORATE; SODIUM CHLORIDE

CareOne Advance Relief Eye Drop (PLD)

Active Ingredient

Dextran 70 0.1%

Polyethylene Glycol 400 1%

Povidone 1%

Tetrahydrozoline HCl 0.5%

Purpose

Lubricant

Lubricant

Lubricant

Redness reliever

Use

- relieves redness of the eye due to minor eye irritations
- as a lubricant to prevent further irritation or to relieve dryness of the eye

Warnings

For external use only

Ask a doctor before using if you have

narrow angle glaucoma

When using this product

- pupils may become enlarged temporarily
- to avoid contamination, do not touch tip of container to any surface. Replace cap after using.
- if solution changes color or becomes cloudy, do not use
- overuse may cause increased redness of the eye
- remove contact lenses before using

Stop use and ask a doctor if

you experience

- eye pain
- changes in vision
- continued redness or irritation of the eye, or if the condition worsens or persists for more than 72 hours

If pregnant or breast-feeding,

ask a health professional before use.

Keep out of reach of children.

If swallowed, get medical help or contact a Poison Control Center right away.

Directions

Instill 1 or 2 drops in the affected eye(s) up to four times daily.

Other information

- store at 15° to 30°C (59°F to 86°F)

Inactive ingredients

benzalkonium chloride, boric acid, edetate disodium, purified water, sodium borate, sodium chloride

package label

Advanced Relief